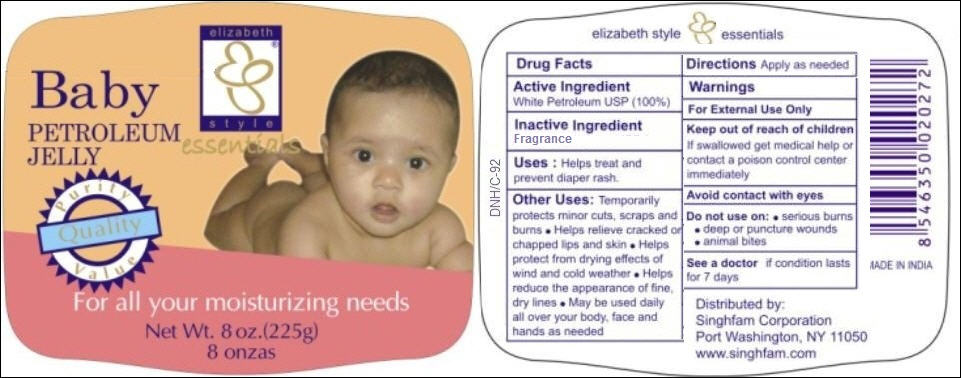 DRUG LABEL: Baby Petroleum
NDC: 52920-122 | Form: JELLY
Manufacturer: Singhfam Corporation
Category: otc | Type: HUMAN OTC DRUG LABEL
Date: 20120120

ACTIVE INGREDIENTS: PETROLATUM 1 g/1 g

Baby Petroleum Jelly

Active Ingredient

100% Petrolatum

Inactive Ingredient

Fragrance

Purpose

Softens Skin and keeps it moisten

Uses:

Helps treat and prevent diaper rash.

Other Uses:

Temporarily protects minor cuts, scraps and burns

- Helps relieve cracked or chapped lips and skin
- Helps protect from drying effects of wind and cold weather
- Helps reduce the appearance of fine, dry lines
- May be used daily all over your body, face and hands as needed

Directions

Apply as needed

Warnings

For external use only.

Keep out of reach of children

If swallowed get medical help or contact a poison control center immediately

Avoid contact with eyes

Do not use on:

- serious burns
- deep or puncture wounds
- animal bites

See a doctor

if condition lasts for 7 days

PACKAGE LABEL

PRINCIPAL DISPLAY PANEL
Elizabeth style essentials
Baby Petroleum Jelly
For all your moisturizing needs
Net Wt. 8 oz. (225 g)
8 onzas